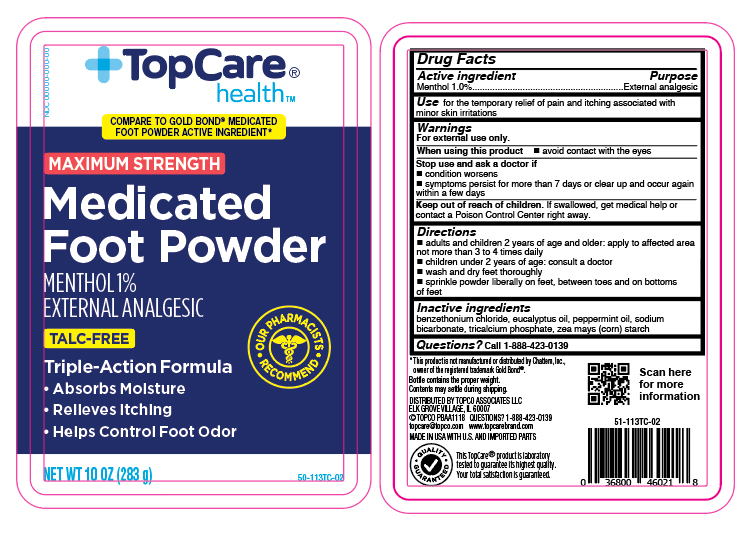 DRUG LABEL: Menthol
NDC: 36800-252 | Form: POWDER
Manufacturer: Topco Associates LLC
Category: otc | Type: HUMAN OTC DRUG LABEL
Date: 20251106

ACTIVE INGREDIENTS: MENTHOL 2.8 g/283 g
INACTIVE INGREDIENTS: ZEA MAYS SUBSP. MAYS WHOLE; TRICALCIUM PHOSPHATE; EUCALYPTUS OIL; SODIUM BICARBONATE; BENZETHONIUM CHLORIDE; PEPPERMINT OIL

Top Care Menthol Foot Powder Talc Free

Active ingredient

Menthol 1.0%

Purpose

External analgesic

Use

for the temporary relief of pain and itching associated with minor skin irritation

Warnings

For external use only.

When using this product

- avoid contact with eyes

Stop and consult a doctor if

- conditions worsens
- symptoms persists for more than 7 days or clear up and occur again within a few days

Keep out of reach of children.

In case of accidental ingestion, get medical help or contact a Poison Control Center right away.

Directions

- adults and children 2 years of age and older, apply to affected area not more than 3 to 4 times daily
- children under 2 years of age, consult a doctor
- wash and dry feet thoroughly
- sprinkle powder liberally on feet, between toes and on bottoms of feet

Inactive ingredients

benzathonium Chloride, eucalyptus oil, peppermint oil, sodium bicarbonate, tricalcium phosphate, zea mays (corn) starch

Questions?

Call - 1-888-423-0139

Principal Display Panel

Top Care health

MAXIMUM STRENGTH

Medicated Foot Powder

MENTHOL 1%

EXTERNAL ANALGESIC

TALC- FREE

Triple-Action Formula

- Absorbs Moisture
- Relieves Itching
- Helps Control Foot Odor

NET WT 10 OZ (283g)